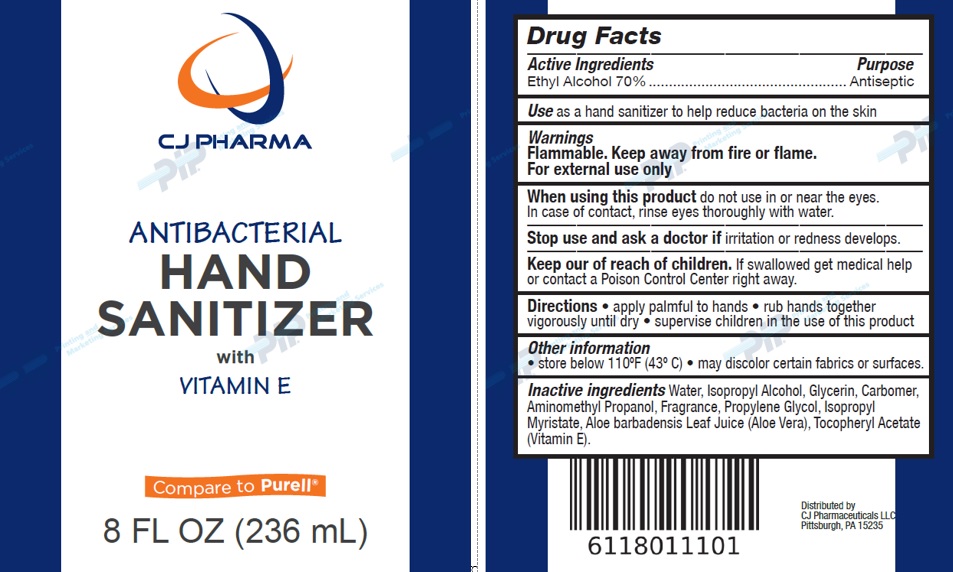 DRUG LABEL: Antibacterial Hand Sanitizer with Vitamine E
                
NDC: 61180-111 | Form: SOLUTION
Manufacturer: CJ Pharmaceuticals, LLC
Category: otc | Type: HUMAN OTC DRUG LABEL
Date: 20160313

ACTIVE INGREDIENTS: ALCOHOL 0.7 mL/1 mL
INACTIVE INGREDIENTS: WATER; ISOPROPYL ALCOHOL; GLYCERIN; CARBOMER INTERPOLYMER TYPE A (ALLYL SUCROSE CROSSLINKED); AMINOMETHYLPROPANOL; PROPYLENE GLYCOL; ISOPROPYL MYRISTATE; ALOE VERA LEAF; .ALPHA.-TOCOPHEROL ACETATE

Antibacterial Hand Sanitizer

Drug Facts

Active Ingredients

Ethyl Alcohol 70%

Purpose

Antiseptic

Use

as hand sanitizer to help reduce bacteria on the skin

Warnings

Flammable. Keep away from fire or flame.
For external use only.

When using this product do not use in or near the eyes. In case of contact, rinse eyes thoroughly with water.

Stop use and ask a doctor if irritation or redness develops.

Keep out of reach of children. If swallowed, get medical help or contact a Poison Control Center right away.

Directions

- apply palmful to hands
- rub hands together vigorously until dry
- supervise children in the use of this product

Other information

- store below 110°F (43°C)
- may discolor certain fabrics or surfaces.

Inactive ingredients

Water, Isopropyl Alcohol, Glycerin, Carbomer, Aminomethyl Propanol, Fragrance, Propylene Glycol, Isopropyl Myristate, Aloe barbadensis Leaf Juice (Aloe Vera), Tocopheryl Acetate (Vitamin E).

Package Label

ANTIBACTERIAL
HAND
SANITIZER with
VITAMIN E
Compare to Purell®
8 FL OZ (236 mL)